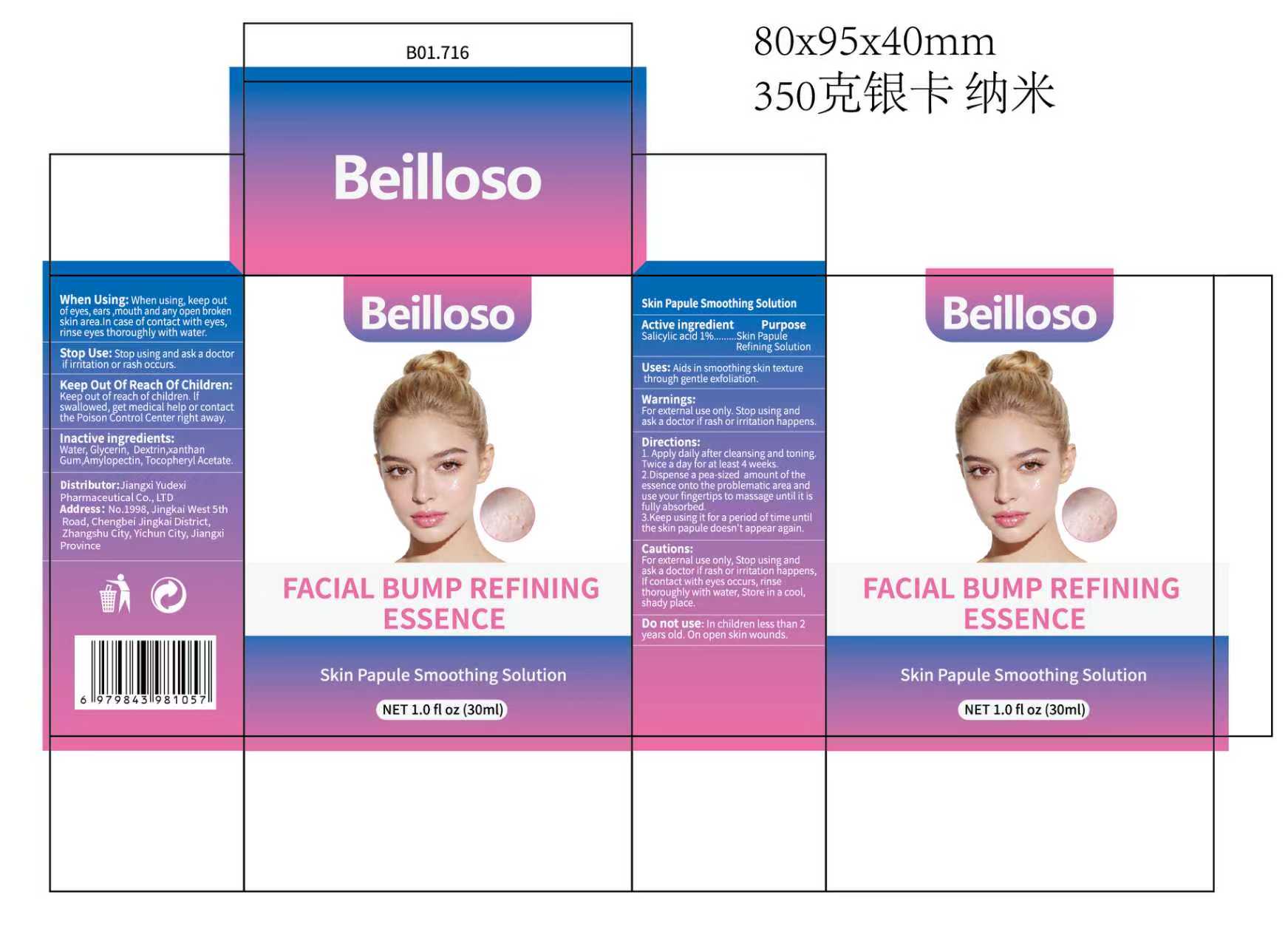 DRUG LABEL: Beilloso FACIAL BUMP REFINING ESSENCE
NDC: 85248-077 | Form: LIQUID
Manufacturer: Jiangxi Yudexi Pharmaceutical Co., LTD
Category: otc | Type: HUMAN OTC DRUG LABEL
Date: 20260207

ACTIVE INGREDIENTS: SALICYLIC ACID 1 g/100 mL
INACTIVE INGREDIENTS: WATER; DEXTRIN, CORN; AMYLOPECTIN, CORN; XANTHAN GUM; GLYCERIN; .ALPHA.-TOCOPHEROL ACETATE

85248-077

Active Ingredient

salicylic acid 1%

Purpose

Skin Papule Refining Solution

Use

Aids in smoothing skin texture through gentle exfoliation.

Warnings

For external use only, Stop using and ask a doctor if rash or irritation happens.

Do not use

In children less than 2 years old. On open skin wounds.

When Using

When using, keep out of eyes, ears ,mouth and any open broken skin area.In case of contact with eyes, rinse eyes thoroughly with water.

Stop Use

Stop using and ask a doctor if irritation or rash occurs.

Ask Doctor

Stop using and ask a doctor if irritation or rash occurs.

Keep Oot Of Reach Of Children

Keep out of reach of children. lf swallowed, get medical help or contact the Poison Control Center right away.

Directions

1. Apply daily after cleansing and toning.Twice a day for at least 4 weeks. 2.Dispense a pea-size amount of the essence onto the problematic area and use your fingertips to massage until it is fully absorbed. 3,Keep using it for a period of time untiL the skin papule doesn't appear again.

Other information

For external use only, Stop using and ask a doctor if rash or irritation happens， lf contact with eyes occurs. rinse thoroughly with water, Store in a cool,shady place.

Inactive ingredients

Water,Glycerin, Dextrin,xanthan Gum,Amylopectin, Tocopheryl Acetate.